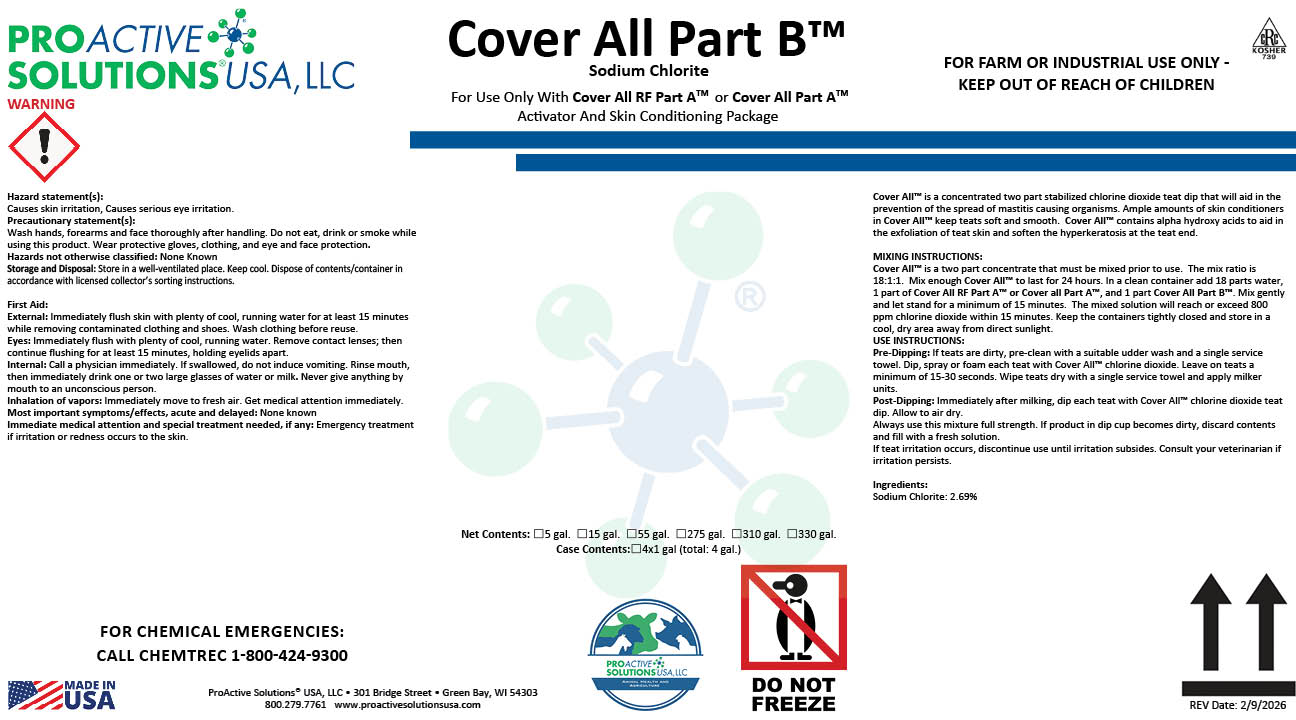 DRUG LABEL: Cover All Part B
NDC: 63927-4118 | Form: LIQUID
Manufacturer: ProActive Solutions USA, LLC
Category: animal | Type: OTC ANIMAL DRUG LABEL
Date: 20260210

ACTIVE INGREDIENTS: SODIUM CHLORITE 10.75 kg/100 kg

Cover All Part B

Cover All Part B

Hazard statement(s):
Causes skin irritation, Causes serious eye irritation.
Precautionary statement(s):
Wash hands, forearms and face thoroughly after handling. Do not eat, drink or smoke while
using this product. Wear protective gloves, clothing, and eye and face protection.
Hazards not otherwise classified: None Known
Storage and Disposal: Store in a well-ventilated place. Keep cool. Dispose of contents/container in
accordance with licensed collector’s sorting instructions.
First Aid:
External: Immediately flush skin with plenty of cool, running water for at least 15 minutes
while removing contaminated clothing and shoes. Wash clothing before reuse.
Eyes: Immediately flush with plenty of cool, running water. Remove contact lenses; then
continue flushing for at least 15 minutes, holding eyelids apart.
Internal: Call a physician immediately. If swallowed, do not induce vomiting. Rinse mouth,
then immediately drink one or two large glasses of water or milk. Never give anything by
mouth to an unconscious person.
Inhalation of vapors: Immediately move to fresh air. Get medical attention immediately.
Most important symptoms/effects, acute and delayed: None known
Immediate medical attention and special treatment needed, if any: Emergency treatment
if irritation or redness occurs to the skin.
Cover All™ is a concentrated two part stabilized chlorine dioxide teat dip that will aid in the
prevention of the spread of mastitis causing organisms. Ample amounts of skin conditioners
in Cover All™ keep teats soft and smooth. Cover All™ contains alpha hydroxy acids to aid in
the exfoliation of teat skin and soften the hyperkeratosis at the teat end.
MIXING INSTRUCTIONS:
Cover All™ is a two part concentrate that must be mixed prior to use. The mix ratio is
18:1:1. Mix enough Cover All™ to last for 24 hours. In a clean container add 18 parts water,
1 part of Cover All RF Part A™ or Cover all Part A™, and 1 part Cover All Part B™. Mix gently
and let stand for a minimum of 15 minutes. The mixed solution will reach or exceed 800
ppm chlorine dioxide within 15 minutes. Keep the containers tightly closed and store in a
cool, dry area away from direct sunlight.
USE INSTRUCTIONS:
Pre-Dipping: If teats are dirty, pre-clean with a suitable udder wash and a single service
towel. Dip, spray or foam each teat with Cover All™ chlorine dioxide. Leave on teats a
minimum of 15-30 seconds. Wipe teats dry with a single service towel and apply milker
units.
Post-Dipping: Immediately after milking, dip each teat with Cover All™ chlorine dioxide teat
dip. Allow to air dry.
Always use this mixture full strength. If product in dip cup becomes dirty, discard contents
and fill with a fresh solution.
If teat irritation occurs, discontinue use until irritation subsides. Consult your veterinarian if
irritation persists.
Ingredients:
Sodium Chlorite: 2.69%